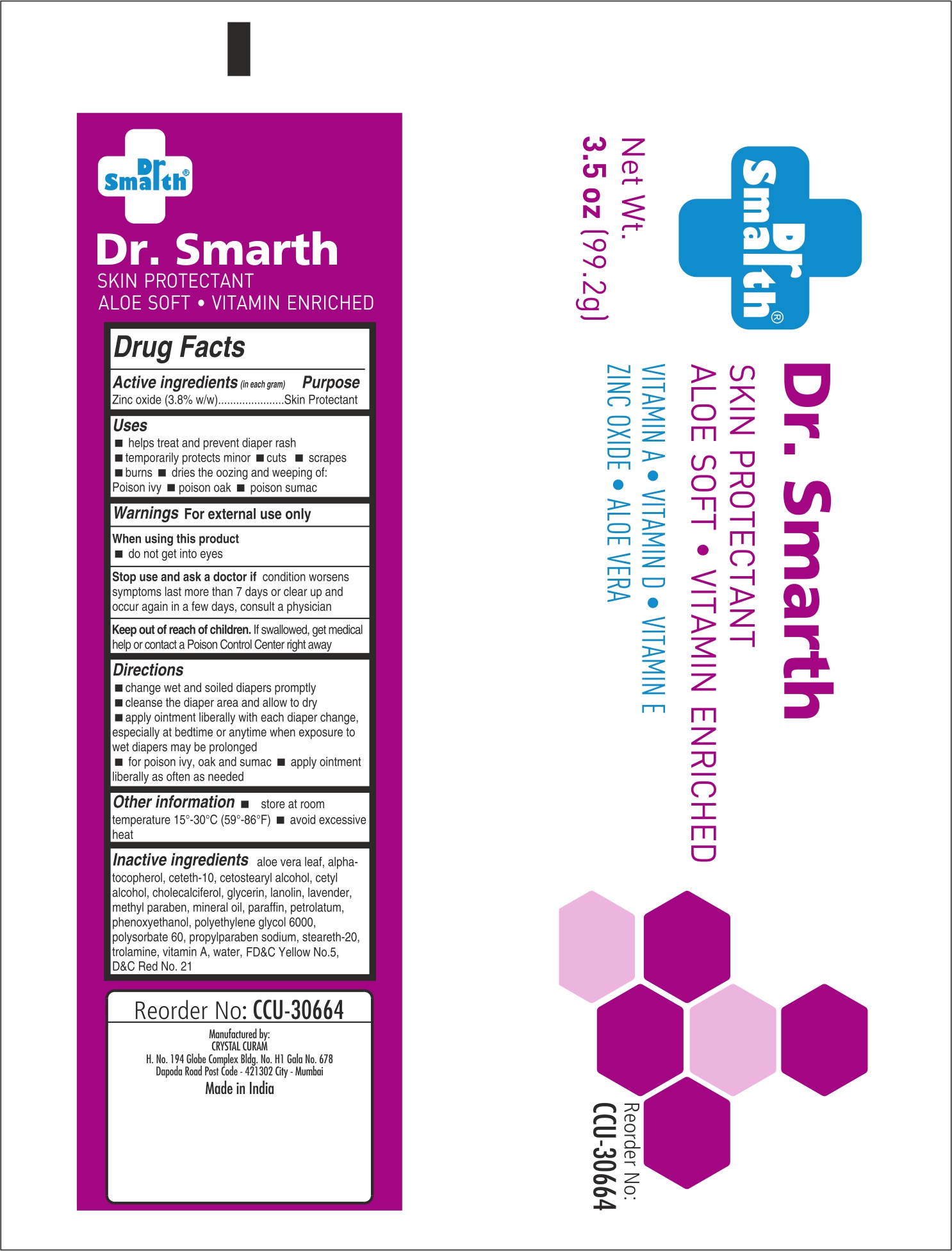 DRUG LABEL: Dr. Smarth
NDC: 72886-3066 | Form: CREAM
Manufacturer: Crystal Curam
Category: otc | Type: HUMAN OTC DRUG LABEL
Date: 20190209

ACTIVE INGREDIENTS: ZINC OXIDE 3.8 g/100 g
INACTIVE INGREDIENTS: ALOE VERA LEAF; ALPHA-TOCOPHEROL; CETETH-10; CETOSTEARYL ALCOHOL; CETYL ALCOHOL; CHOLECALCIFEROL; GLYCERIN; LANOLIN; LAVENDER OIL; METHYLPARABEN; MINERAL OIL; PARAFFIN; PETROLATUM; PHENOXYETHANOL; POLYETHYLENE GLYCOL 6000; POLYSORBATE 60; PROPYLPARABEN SODIUM; STEARETH-20; TROLAMINE; VITAMIN A; WATER; FD&C YELLOW NO. 5; D&C RED NO. 21

Dr. Smarth Enshield

Active Ingredient

Zinc Oxide (3.8%w/w)

Purpose

Skin Protectant

Uses

■ helps treat and prevent diaper rash ■ temporarily protects minor ■ cuts ■ scrapes ■ burns dries the oozing and weeping of: ■ Poison ivy ■ poison oak ■ poison sumac

Warnings

For external use only

When using this product

■ do not get into eyes

Stop Use and ask a doctor if

conditions worsen symptoms last more than 7 days or clear up and occur again in a few days, consult a physician

Keep out of reach of children

If swallowed, get medical help or contact a Poison Control Center right away.

Directions

■ change wet and soiled diapers promptly ■ cleanse the diaper area and allow to dry ■ apply ointment liberally with each diaper change, especially at bedtime or anytime when exposure to wet diapers may be prolonged ■ for poison ivy, oak and sumac ■ apply ointment liberally as needed

Other Information

■ store at room temperature 15-30C (59-86F) ■ avoid excessive heat

Inactive ingredients

aloe vera leaf, alpha-tocopherol, ceteth-10, cetostearyl alcohol, cetyl alcohol, cholecalciferol, glycerin, lanolin, lavender
methylparaben, mineral oil, paraffin, petrolatum, phenoxyethanol, polyethylene glycol 6000, polysorbate 60, propylparaben sodium
steareth-20, trolamine, vitamin A, water, FDC Yellow No.5, DC Red No.21